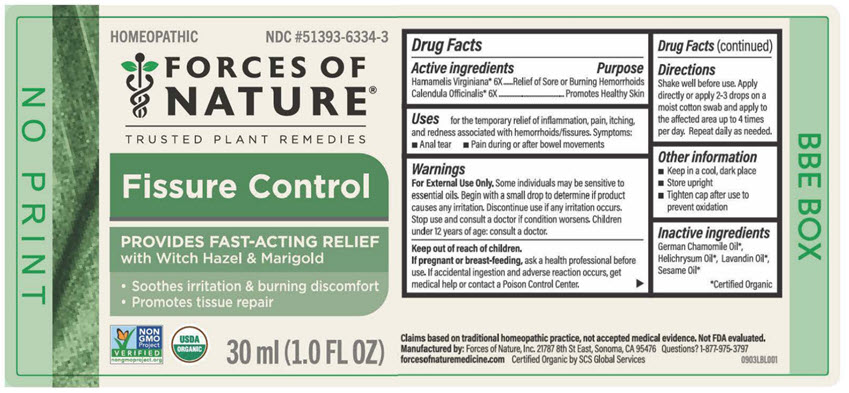 DRUG LABEL: Fissure Control
NDC: 51393-6334 | Form: SOLUTION/ DROPS
Manufacturer: Forces of Nature
Category: homeopathic | Type: HUMAN OTC DRUG LABEL
Date: 20251125

ACTIVE INGREDIENTS: CALENDULA OFFICINALIS FLOWERING TOP 6 [hp_X]/100 mL; HAMAMELIS VIRGINIANA ROOT BARK/STEM BARK 6 [hp_X]/100 mL
INACTIVE INGREDIENTS: CHAMOMILE FLOWER OIL; Lavandin Oil; Sesame Oil; HELICHRYSUM ITALICUM FLOWER OIL

Fissure Control

DRUG FACTS

ACTIVE INGREDIENT

PURPOSE

Active Ingredients

Hamamelis Virginiana [USDA Certified Organic] 6X - Relief of Hemorrhoids that are Sore or Burning

Calendula Officinalis 6X - Promotes Healthy Skin

Also Contains

Sesame Oil, Helichrysum Oil, German Chamomile Oil, Lavandin Oil

Indications

For the relief of inflammation, pain, itching and redness associated with hemorrhoids/fissures. Symptoms of fissures include an anal tear, pain during or after bowel movements, blood in the stool.

Directions

Shake well before use. Dab 2-3 drops of oil to treatment area 2-4 times per day; apply daily until problem is gone. For children under 2 years of age, consult a doctor before use.

Warnings

Do not put this product into the rectum by using fingers or any mechanical device or applicator. Some individuals may be sensitive to essential oils. Begin with a small drop to determine if the product causes any increased redness or irritation and discontinue use if it irritates your skin. For external use only. If accidental ingestion of more than several drops, and adverse reaction occurs, get medical help or contact a Poison Control Center. Do not apply to the eyes. If you are pregnant or breast-feeding, ask a health professional before use. Not for use on children under the age of 2 without physician direction.

KEEP OUT OF REACH OF CHILDREN

Keep all medicines out of the reach of children.

Stop use and consult a doctor if condition worsens, or consult a doctor if symptoms show no improvement after 7 days.

Tips For Use

Fissure Control's soothing ingredients offer immediate relief from pain and discomfort caused by fissures. It also quickly repairs the damaged tissue and encourages your body to heal itself faster than it would be able to without the medicine.

The pain relief can often be felt immediately. Torn skin is typically healed within one week, but more severe cases may require longer treatment time. The healing time can be made longer or shorter, depending on a few factors including:

- Constipation and straining during bowel movements.
- The length of time your fissure has existed - The longer the symptom has been present the longer the treatment will take.
- Your application schedule - Fissure Control should be applied at least 2-3 times every day while the symptom exists.

Manufactured by:
Forces of Nature, Inc.
21787 8th St East #3A
Sonoma, CA 95476 USA

PRINCIPAL DISPLAY PANEL - 30 ml Bottle Label

HOMEOPATHIC
NDC #51393-6334-3

FORCES OF
NATURE®

TRUSTED PLANT REMEDIES

Fissure Control

PROVIDES FAST-ACTING RELIEF
with Witch Hazel & Marigold

- Soothes irritation & burning discomfort
- Promotes tissue repair

NON
GMO
Project
VERIFIED
nongmoproject.org

USDA
ORGANIC

30 ml (1.0 FL OZ)